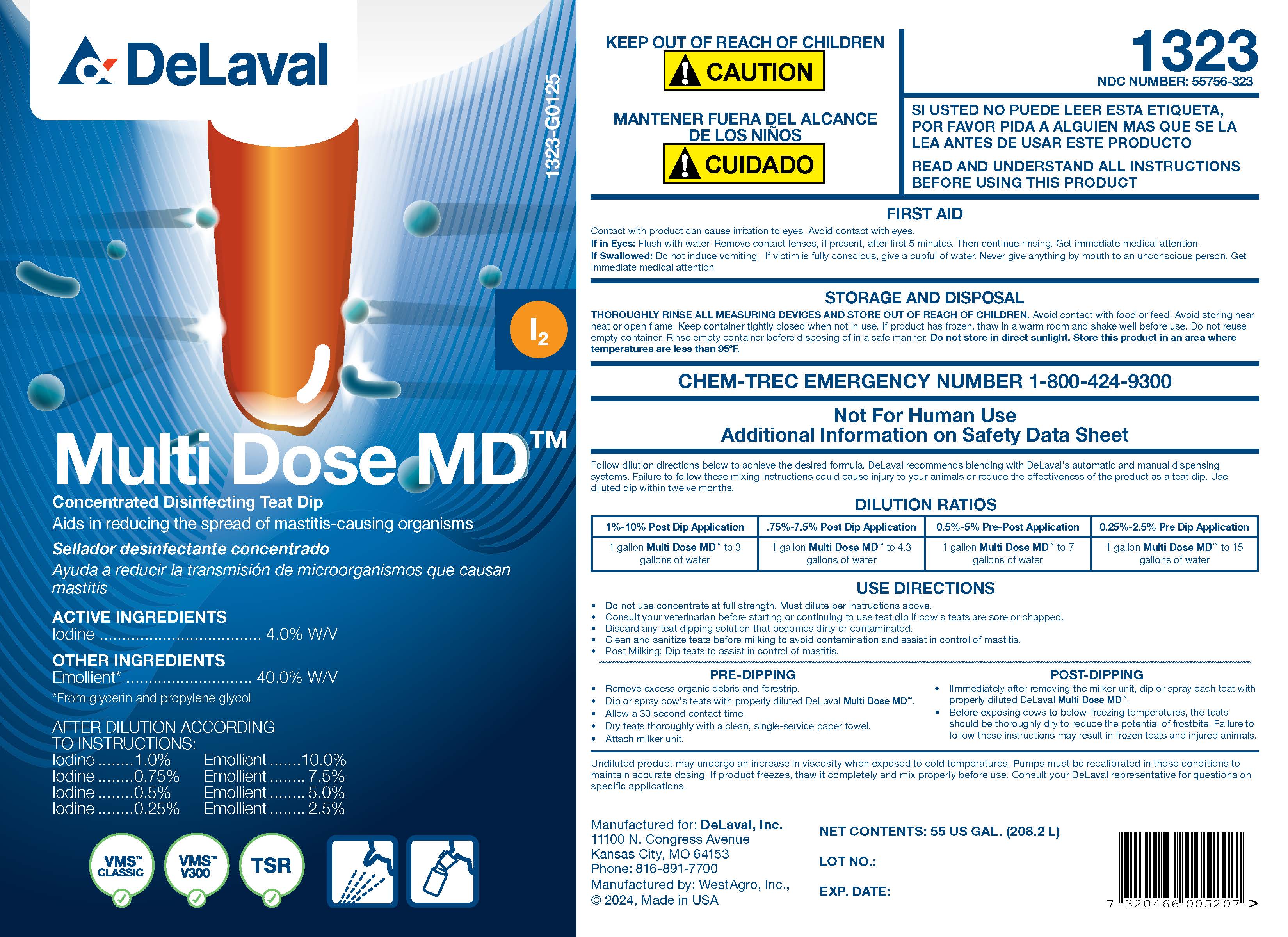 DRUG LABEL: Multi Dose MD
NDC: 55756-323 | Form: SOLUTION, CONCENTRATE
Manufacturer: DeLaval
Category: animal | Type: OTC ANIMAL DRUG LABEL
Date: 20250302

ACTIVE INGREDIENTS: IODINE 4000 mg/1 L
INACTIVE INGREDIENTS: GLYCERIN; C9-11 PARETH-8; POLOXAMER 335; PROPYLENE GLYCOL; SODIUM IODIDE; ANHYDROUS CITRIC ACID; SODIUM HYDROXIDE; WATER

DeLaval Multi Dose MD™

PURPOSE

Concentrated Disinfecting Teat Dip
Aids in reducing the spread of mastitis-causing organisms

Sellador Concentrado Para Pezones
Ayuda a reducir la transmission de microoganismsos que causan mastis

ACTIVE INGREDIENTS
Iodine........................................4.0% W/V

OTHER INGREDIENTS

Emollient* ..................... 40.0% W/V

*From glycerin and propylene glycol

AFTER DILUTION ACCORDING TO INSTRUCTIONS:

Iodine..........1.0% Emollient..........10.0%

Iodine..........0.75% Emollient.......... 7.5%

Iodine..........0.5% Emollient.......... 5.0%

Iodine..........0.25% Emollient.......... 2.5%

KEEP OUT OF REACH OF CHILDREN
! CAUTION

MANTENER FUERA DEL ALCANCE DE LOS NINOS
! CUIDADO

1323
NDC NUMBER: 55756-323

WARNINGS

SI USTED NO PUEDE LEER ESTA ETIQUETA, POR FAVOR PIDA A ALGUIEN MAS QUE SE LA LEA ANTES DE USAR ESTE PRODUCTO

READ AND UNDERSTAND ALL INSTRUCTIONS BEFORE USING THIS PRODUCT

FIRST AID
Contact with product can cause irritation to eyes. Avoid contact with eyes.
If in Eyes: Flush with water. Remove contact lenses, if present, after first 5 minutes. Then continue rinsing. Get immediate medical attention.
If Swallowed: Do not induce vomiting. If victim is fully conscious, give a cupful of water. Never give anything my mouth to an unconscious person. Get immediate medical attention.

STORAGE AND DISPOSAL
THOROUGHLY RINSE ALL MEASURING DEVICES AND STORE OUT OF REACH OF CHILDREN. Avoid contact with food or feed. Avoid storing near heat or open flame. Keep container tightly closed when not in use. If product has frozen, thaw in a warm room and shake well before use. Do not reuse empty container. Rinse empty container before disposing of in a safe manner. Do not store in direct sunlight. Store this product in an area where temperatures are less than 95°F.

CHEM-TREC EMERGENCY NUMBER 1-800-424-9300

Not for Human Use
Additional Information on Safety Data Sheet

Follow dilution directions below to achieve the desired formula. DeLaval recommends blending with DeLaval's automatic and manual dispensing systems. Failure to follow these mixing instructions could cause injury to your animals or reduce the effectiveness of the product as a teat dip. Use diluted dip within twelve months.

DILUTION RATIOS
1%-10% Post Dip Application | .75%-7.5% Post Dip Application | 0.5%-5% Pre-Post Application | 0.25%-2.5% Pre Dip Application
1 gallon Multi Dose MD™ to 3 gallons of water | 1 gallon Multi Dose MD™ to 4.3 gallons of water | 1 gallon Multi Dose MD™ to 7 gallons of water | 1 gallon Multi Dose MD™ to 15 gallons of water

DOSAGE AND ADMINISTRATION

USE DIRECTIONS

- Do not use concentrate at full strength. Must dilute per instructions above.
- Consult your veterinarian before starting or continuing to use teat dip if cow's teats are sore or chapped.
- Discard any teat dipping solution that becomes dirty or contaminated.
- Clean and sanitize teats before milking to avoid contamination and assist in control of mastitis.
- Post Milking: Dip teats to assist in control of mastitis.

PRE-DIPPING

- Remove excess organic debris and forestrip.
- Dip or spray cow's teats with properly diluted DeLaval Multi Dose MD™ .
- Allow a 30 second contact time.
- Dry teats thoroughly with a clean, single-service paper towel.
- Attach milker unit.

POST-DIPPING

- Immediately after removing the milker unit, dip or spray each teat with properly diluted DeLaval Multi Dose MD™.
- Before exposing cows to below-freezing temperatures, the teats should be thoroughly dry to reduce the potential of frostbite. Failure to follow these instructions may result in frozen teats and injured animals.

Undiluted product may undergo an increase in viscosity when exposed to cold temperatures. Pumps must be recalibrated in those conditions to maintain accurate dosing. If product freezes, thaw it completely and mix properly before use. Consult your DeLaval representative for questions on specific applications.

NET CONTENTS: US GAL. (L)

LOT NO.:

EXP. DATE:

Manufactured for: DeLaval, Inc.
11100 N. Congress Avenue
Kansas City, MO 64153
Phone: 816-891-7700
Manufactured by: WestAgro, Inc.,
©2024, Made in USA

PACKAGE LABEL

Add image transcription here...